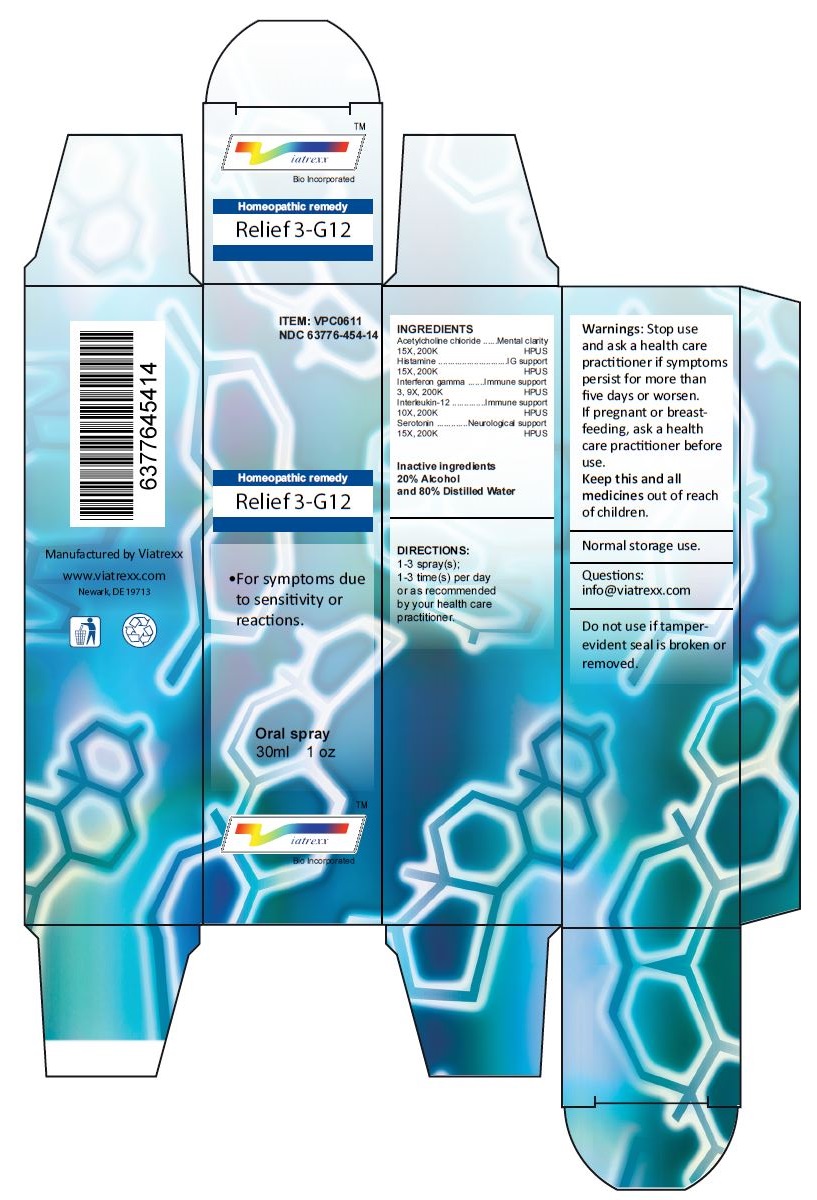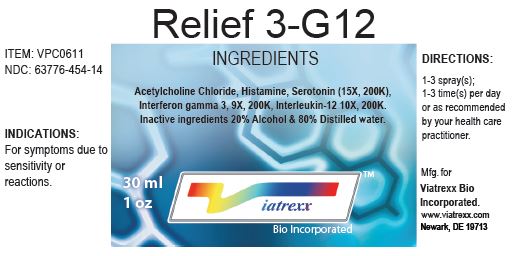 DRUG LABEL: Relief 3-G12
NDC: 63776-454 | Form: SPRAY
Manufacturer: VIATREXX BIO INCORPORATED
Category: homeopathic | Type: HUMAN OTC DRUG LABEL
Date: 20221130

ACTIVE INGREDIENTS: ACETYLCHOLINE CHLORIDE 200 [kp_C]/1 mL; HISTAMINE 200 [kp_C]/1 mL; INTERFERON GAMMA-1A 200 [kp_C]/1 mL; INTERLEUKIN-12 HUMAN 200 [kp_C]/1 mL; SEROTONIN 200 [kp_C]/1 mL
INACTIVE INGREDIENTS: WATER; ALCOHOL

Relief 3-G12

Active Ingredients

Acetylcholine chloride (15X, 200K), Histamine (15X 200K), Interferon gamma (3, 9X, 200K), Interleukin-12 (10X, 200K), Serotonin (15X 200K)

Purpose:

Acetylcholine chloride | Mental clarity
Histamine | IG support
Interferon gamma | Immune support
Interleukin-12 | Immune support
Serotonin | Neurological support

Uses

For symptoms due to sensitivity or reactions.

Warnings

Stop use and ask a health care practitioner if symptoms persist for more than five days or worsen. If pregnant or breastfeeding, ask a health care practitioner before use.

Dosage

1-3 spray(s); 1-3 time(s) per day or as recommended by your health care practitioner.

KEEP OUT OF REACH OF CHILDREN

Keep this and all medicines out of reach of children.

Inactive Ingredients

20% Alcohol and 80% Water

Other Information

Normal storage use.
Do not use if tamper-evident seal is broken or removed.

Questions

info@viatrexx.com

Principal Display Panel

VPC0611
NDC 63776-454-14
Homeopathic remedy
Relief 3-G12
• For symptoms due to sensitivity or reactions.
Oral spray
30ml 1 oz
Viatrexx™ Bio Incorporated
Manufactured by Viatrexx
www.viatrexx.com
Newark, DE 19713

Relief 3-G12
30 mL
1 oz
Viatrexx™ Bio Incorporated
ITEM: VPC0611
NDC: 63776-454-14
INDICATIONS:
For symptoms due to sensitivity or reactions.
DIRECTIONS:
1-3 spray(s); 1-3 time(s) per day or as recommended by your health care practitioner.
Mfg. for
Viatrexx Bio Incorporated.
www.viatrexx.com
Newark, DE 19713